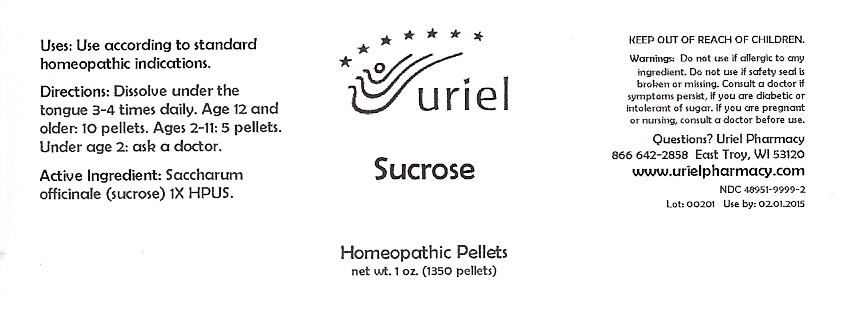 DRUG LABEL: Sucrose
NDC: 48951-9999 | Form: PELLET
Manufacturer: Uriel Pharmacy Inc
Category: homeopathic | Type: HUMAN OTC DRUG LABEL
Date: 20100202

ACTIVE INGREDIENTS: SUCROSE 1 [hp_X]/1 1

Sucrose Pellets - 1 oz.

Purpose

Uses: Use according to standard homeopathic indications.

Dosage & Administration

Directions: Dissolve under the tongue 3-4 times daily. Age 12 and older: 10 pellets. Ages 2-11: 5 pellets. Under age 2: ask a doctor.

OTC-Active Ingredient

Active Ingredient: Saccharum officinale (sucrose) 1X HPUS.

Keep out of reach of children

Do not use section

Warnings: Do not use if allergic to any ingredient. Do not use if safety seal is broken or missing.

Ask doctor section

Consult a doctor if symptoms persist, if you are diabetic or intolerant of sugar.

Pregnancy or breast feeding section

If you are pregnant or nursing, consult a doctor before use.

Questions section

Questions? Uriel Pharmacy

866 642-2858 East Troy, WI 53120

www.urielpharmacy.com

NDC 48951-9999-2

Principal Display Panel

Sucrose

Homeopathic Pellets

net wt. 1 oz. (1350 pellets)